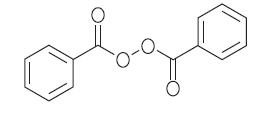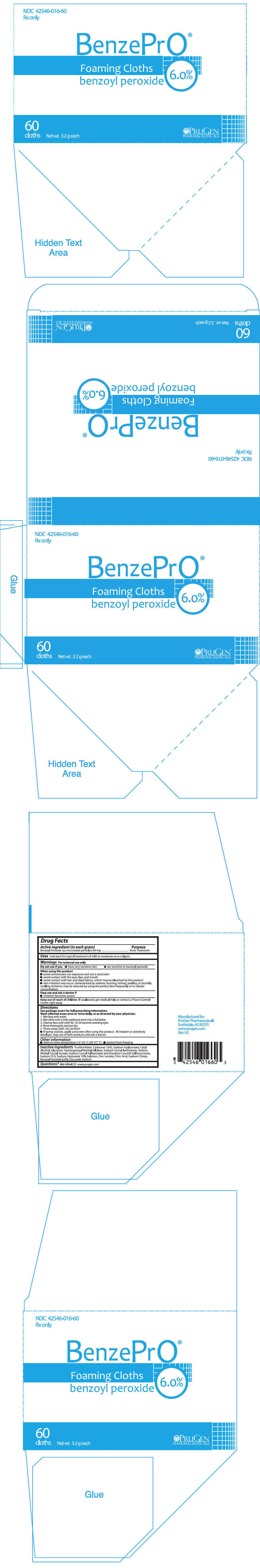 DRUG LABEL: BenzePrO
NDC: 42546-016 | Form: CLOTH
Manufacturer: PruGen, Inc.
Category: prescription | Type: HUMAN PRESCRIPTION DRUG LABEL
Date: 20220119

ACTIVE INGREDIENTS: Benzoyl Peroxide 60 mg/1 1
INACTIVE INGREDIENTS: water; Carbomer Copolymer Type B (Allyl Pentaerythritol Crosslinked); Hyaluronate Sodium; Cetyl Alcohol; Glycerin; HYPROMELLOSE 2910 (15 MPA.S); Sodium Cocoyl Isethionate; Sodium Methyl Cocoyl Taurate; Sodium Lauryl Sulfoacetate; Disodium Laureth Sulfosuccinate; Sodium Pyrrolidone Carboxylate; Sodium Hydroxide; Zinc Lactate; Citric Acid Monohydrate; Sodium Citrate, Unspecified Form; Docusate Sodium

BenzePrO®
Foaming Cloths
benzoyl peroxide 6.0%

Rx Only

DESCRIPTION

BenzePrO® Foaming Cloths are a topical preparation containing 6.0% benzoyl peroxide. Each gram of BenzePrO® Foaming Cloths wash contains 60 mg of Benzoyl Peroxide as micronized particles. Ingredients include Purified Water, Carbomer 1342, Sodium Hyaluronate, Cetyl Alcohol, Glycerine, Hydroxypropyl Methylcellulose, Sodium Cocoyl Isethionate, Sodium Methyl Cocoyl Taurate, Sodium Lauryl Sulfoacetate and Disodium Laureth Sulfosuccinate, Sodium PCA, Sodium Hydroxide 10% Solution, Zinc Lactate, Citric Acid, Sodium Citrate, Benzoyl Peroxide 6.0%, Docusate Sodium.

Benzoyl peroxide is an oxidizing agent that possesses antibacterial properties and is classified as a keratolytic. Benzoyl peroxide (C14H10O4) is represented by the following structure:

CLINICAL PHARMACOLOGY

The exact method of action of benzoyl peroxide in acne vulgaris is not known. Benzoyl peroxide is an antibacterial agent with demonstrated activity against Propionibacterium acnes. This action, combined with the mild keratolytic effect of benzoyl peroxide, is believed to be responsible for its usefulness in acne. Benzoyl peroxide is absorbed by the skin where it is metabolized to benzoic acid and excreted as benzoate in the urine.

INDICATIONS AND USAGE

BenzePrO® Foaming Cloths are indicated for use in the topical treatment of mild to moderate acne vulgaris.

CONTRAINDICATIONS

BenzePrO® Foaming Cloths should not be used in patients who have shown hypersensitivity to benzoyl peroxide or to any of the other ingredients in the product. Discontinue use if hypersensitivity is observed.

WARNINGS

FOR EXTERNAL USE ONLY. Not For Ophthalmic Use. Keep out of the reach of children. If swallowed, get medical help or contact a Poison Control Center right away.

When using this product, skin irritation and dryness is more likely to occur if:

- you leave BenzePrO® Foaming Cloths on your skin longer than directed
- you use another topical acne medication at the same time

Do not use this product if you:

- have very sensitive skin
- are sensitive to benzoyl peroxide

When using this product:

- avoid unnecessary sun exposure and use a sunscreen
- avoid contact with the eyes, lips, mouth
- avoid contact with hair and dyed fabrics, which may be bleached by this product
- skin irritation may occur, characterized by redness, burning, itching, peeling, or possibly swelling. Irritation may be reduced by using the product less frequently or in lower concentration.

Stop use and ask a doctor:

- if irritation becomes severe.

PRECAUTIONS

General

If severe irritation develops, discontinue use and institute appropriate therapy.

Information for patients

This medication is to be used as directed by a physician and should not be used to treat any condition other than that for which it was prescribed. Avoid contact with eyes, eyelids, lips, and mucous membranes. If accidental contact occurs, rinse with water. If excessive redness or irritation develops, discontinue use and consult your physician.

Carcinogenesis, Mutagenesis, Impairment of Fertility

Based upon all available evidence, benzoyl peroxide is not considered to be a carcinogen. However, data from a study using mice known to be highly susceptible to cancer suggest that benzoyl peroxide acts as a tumor promoter. The clinical significance of the findings is not known.

Pregnancy

Category C animal reproduction studies have not been conducted with benzoyl peroxide. It is also not known whether benzoyl peroxide can cause fetal harm when administered to a pregnant woman or can affect reproduction capacity. Benzoyl peroxide should be used by a pregnant woman only if clearly needed.

Nursing Mothers

It is not known whether this drug is excreted in the human milk. Because many drugs are excreted in human milk, caution should be exercised when benzoyl peroxide is administered to a nursing woman.

Pediatric Use

Safety and effectiveness in children below the age of 12 have not been established.

ADVERSE REACTIONS

Allergic contact dermatitis and dryness have been reported with topical benzoyl peroxide therapy.

OVERDOSAGE

If excessive scaling, erythema or edema occurs, the use of this preparation should be discontinued. To hasten resolution of the adverse effects, cool compresses may be used. After symptoms and signs subside, a reduced dosage schedule may be cautiously tried if the reaction is judged to be due to excessive use and not allergenicity.

DIRECTIONS

Avoid contact with hair, fabrics or carpeting as benzoyl peroxide will cause bleaching or discoloration.

Wash affected areas once or twice daily, or as directed by your physician.

1. Wet face with water.
2. Wet cloth with a little waterand work into a full lather.
3. Cleanse face with cloth for 10-20 seconds avoiding eyes.
4. Rinse thoroughly and pat dry.
5. Throw away cloth. Do not flush.

- If going outside, apply sunscreen after using this product. If irritation or sensitivity develops, stop use of both products and ask a doctor.

HOW SUPPLIED

BenzePrO® Foaming Cloths are supplied in a carton containing 60 × 3.2 g individually wrapped benzoyl peroxide 6% foaming cloths (NDC 42546-016-60).

STORAGE AND HANDLING

Store at room temperature: 15° - 25°C (59° - 77°F). Protect from freezing.

Manufactured for:
PruGen Pharmaceuticals
18899 N Thompson Peak Pkwy
Scottsdale, AZ 85255
www.prugen.com

Rev. 3.0

PRINCIPAL DISPLAY PANEL - 60 Cloth Packet Carton

NDC 42546-016-60
Rx only

BenzePrO®

Foaming Cloths
benzoyl peroxide 6.0%

60
cloths
Net wt. 3.2 g each

PRUGEN
PHARMACEUTICALS